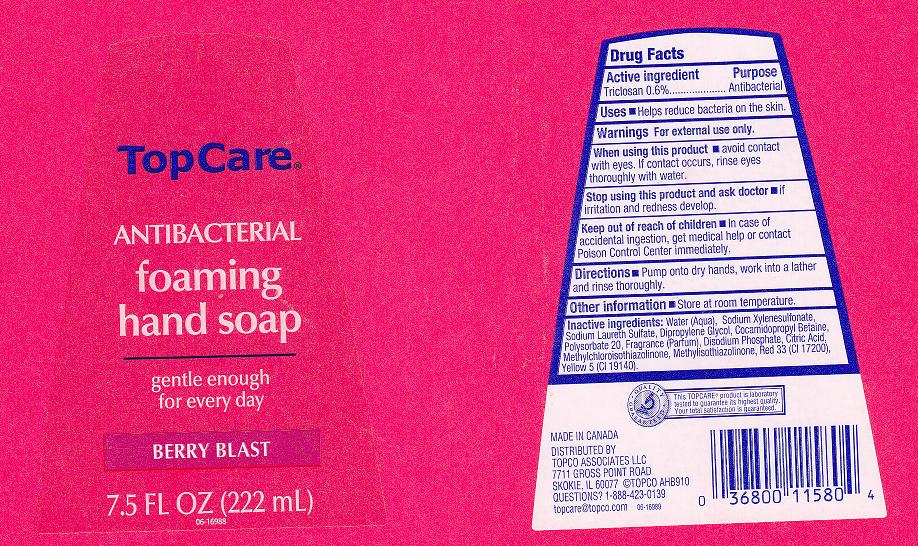 DRUG LABEL: ANTIBACTERIAL FOAMING 
NDC: 36800-076 | Form: LIQUID
Manufacturer: TOPCO ASSOCIATES LLC
Category: otc | Type: HUMAN OTC DRUG LABEL
Date: 20111102

ACTIVE INGREDIENTS: TRICLOSAN 0.6 mL/100 mL
INACTIVE INGREDIENTS: SODIUM XYLENESULFONATE; DIPROPYLENE GLYCOL; SODIUM LAURETH SULFATE; COCAMIDOPROPYL BETAINE; SODIUM PHOSPHATE, DIBASIC, DIHYDRATE; CITRIC ACID MONOHYDRATE; D&C RED NO. 33; FD&C YELLOW NO. 5; WATER; POLYSORBATE 20; METHYLCHLOROISOTHIAZOLINONE; METHYLISOTHIAZOLINONE

DRUG FACTS

ACTIVE INGREDIENT

TRICLOSAN 0.6 PERCENT

PURPOSE

ANTIBACTERIAL

USES

HELPS REDUCE BACTERIA ON THE SKIN.

WARNINGS

FOR EXTERNAL USE ONLY.

KEEP OUT OF REACH OF CHILDREN

IN CASE OF ACCIDENTAL INGESTION, GET MEDICAL HELP OR CONTACT A POISON CONTROL CENTER IMMEDIATELY.

WHEN USING THIS PRODUCT

AVOID CONTACT WITH EYES.IF CONTACT OCCURS, RINSE EYES THOROUGHLY WITH WATER.

STOP USING THIS PRODUCT AND ASK DOCTOR IF

IRRITATION AND REDNESS DEVELOPS AND LASTS.

DIRECTIONS

PUMP ONTO DRY HANDS, WORK INTO A LATHER AND RINSE THOROUGHLY.

STORAGE AND HANDLING

STORE AT ROOM TEMPERATURE.

INACTIVE INGREDIENTS

WATER, SODIUM XYLENESULFONATE, SODIUM LAURETH SULFATE, DIPROPYLENE GLYCOL, COCAMIDOPROPYL BETAINE, POLYSORBATE 20, FRAGRANCE, DISODIUM PHOSPHATE, CITRIC ACID, METHYLCHLOROISOTHIAZOLINONE, METHYLISOTHIAZOLINONE, RED 33 (CI 17200), YELLOW 5 (CI 19140).